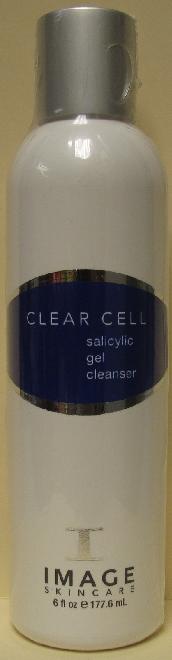 DRUG LABEL: Clear Cell Cleanser
NDC: 62742-4045 | Form: GEL
Manufacturer: Allure Labs, Inc.
Category: otc | Type: HUMAN OTC DRUG LABEL
Date: 20100728

ACTIVE INGREDIENTS: SALICYLIC ACID 30 mg/1 mL

Drug Facts

INDICATIONS AND USAGE SECTION:

A daily Salicylic acid cleanser that exfoiates, gently removes makeup and diminishes excess oil. Anti-oxidants keep skin soft, purified and shine-free.

Paraben free

DIRECTIONS:

Apply to wet face and massage for 1 minute. Repeat cleansing for additional exfoliation.

INDICATIONS:

Acne and acne-prone skin

ACTIVE INGREDIENTS:

Salicylic Acid

INACTIVE INGREDIENTS:

Water (Aqua), Ammonium Laureth Sulfate, Disodium cocoamphodiacetate, Glycerin, PEG 120 Methyl Glucose Dioleate, Phenoxyethanol, Caprylyl Glycol, Camellia sinensis (Green Tea) leaf extract, Ethylhexylglycerin, Polyquaternium-10, Hexylene Glycol, Arnica montana (Arnica) flower extract, Chamomilla recutita (Chamomile) flower extract, Aesculus hippocastanum (Horse Chestnut) extract, Melia azadirachta (neem) leaft extract, Hamamelis virginiana (Witch Hazel) water, Melaleuca alternifolia (Tea Tree) leaf oil, Mentha viridis (spearmint) oil, Eucalyptus globulus (Eucalyptus) leaf oil.

PACKAGE LABEL

DISTRIBUTOR:

Image International

Palm Beach, FL 33411 USA

IMAGE OF PRINCIPAL DISPLAY PANEL: